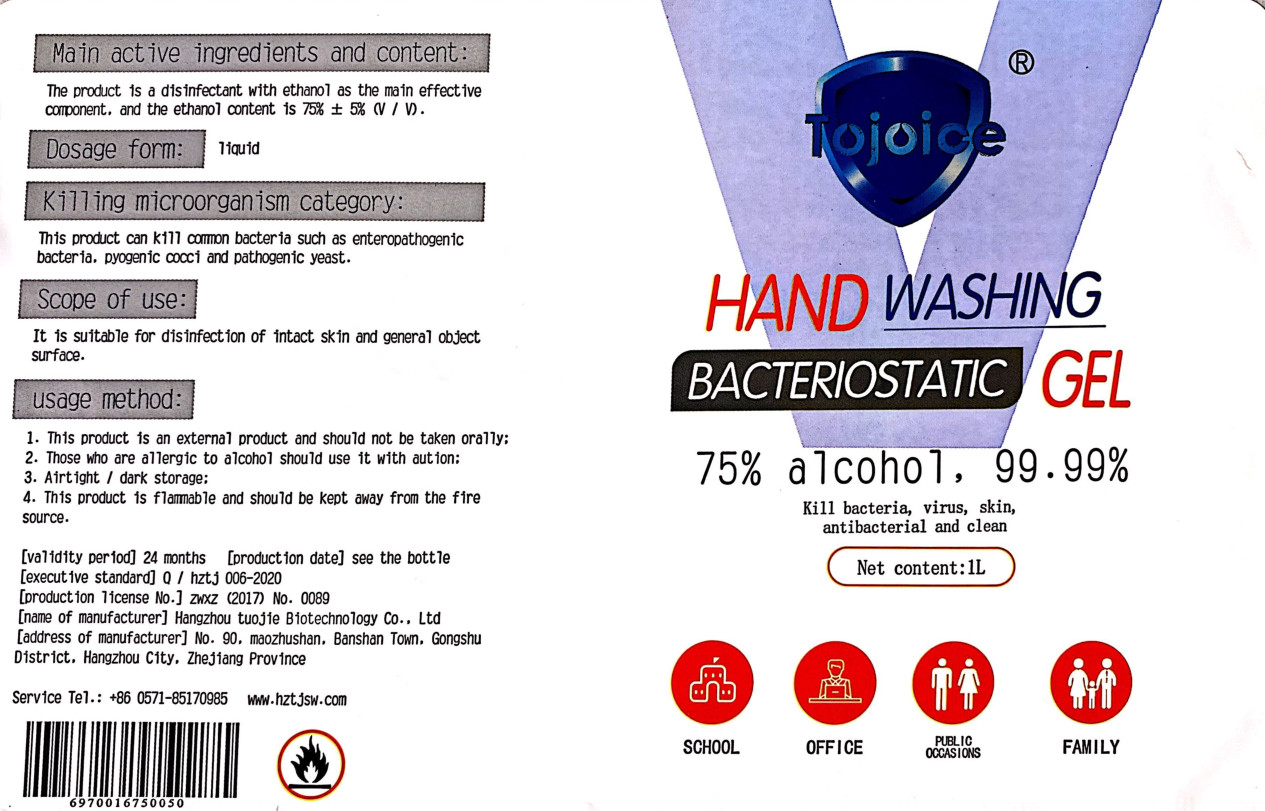 DRUG LABEL: Hand-washing antibacterial gel
NDC: 62178-003 | Form: LIQUID
Manufacturer: Hangzhou Tuojie Biotechnology Co.,Ltd.
Category: otc | Type: HUMAN OTC DRUG LABEL
Date: 20200608

ACTIVE INGREDIENTS: ALCOHOL 750 mL/1000 mL
INACTIVE INGREDIENTS: CARBOMER HOMOPOLYMER, UNSPECIFIED TYPE; TROLAMINE; GLYCERIN; ALOE; WATER

DOSAGE AND ADMINISTRATION

Airtight / dark storage

INACTIVE INGREDIENT

carbomer, triethanolamine, aloe extract, glycerin, deionized water

INDICATIONS AND USAGE

Place enough product on hands to cover all surfaces. Rub hands together until dry.

ACTIVE INGREDIENT

75% ethanol

keep out of reach of children

PURPOSE

Disinfection
Sterilization
No Rinseing

WARNINGS

1. This product is an external product and should not be taken orally;
2. Those who are allergic to alcohol should use it with aution;
3. Airtight / dark storage;
4. This product is flammable and should be kept away from the fire source.